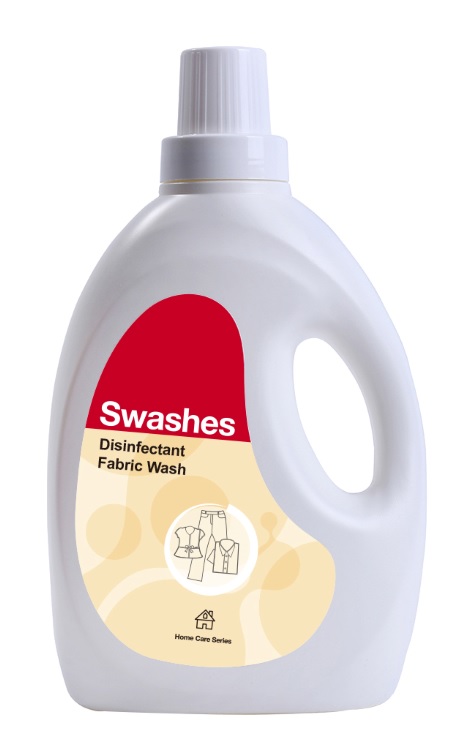 DRUG LABEL: Disinfectant Fabric Wash
NDC: 74974-012 | Form: LIQUID
Manufacturer: Swashes (Shenzhen) Co., Ltd.
Category: otc | Type: HUMAN OTC DRUG LABEL
Date: 20200413

ACTIVE INGREDIENTS: CHLORHEXIDINE ACETATE 0.5 g/1 L
INACTIVE INGREDIENTS: WATER; SODIUM ACETATE ANHYDROUS; SODIUM ACETATE; C12-15 PARETH-10; COCO DIETHANOLAMIDE

Disinfectant Fabric Wash 74974-012

Disinfectant Fabric Wash

Active Ingredient(s)

CHLORHEXIDINE ACETATE

Purpose: Antiseptic

Purpose

Antiseptic, Disinfectant Fabric Wash

Use

Adding when washing clothes can kill bacteria

Warnings

For external use only. Flammable. Keep away from heat or flame

Do not use

- in children less than 2 months of age
- on open skin wounds

When using this product keep out of eyes, ears, and mouth. In case of contact with eyes, rinse eyes thoroughly with water.
Stop use and ask a doctor if irritation or rash occurs. These may be signs of a serious condition.
Keep out of reach of children. If swallowed, get medical help or contact a Poison Control Center right away.

Stop use and ask a doctor if irritation or rash occurs. These may be signs of a serious condition.

Keep out of reach of children. If swallowed, get medical help or contact a Poison Control Center right away.

Directions

- European Washer half-load 1/5 CUP full-load 1/2 CUP

Other information

- Store between 15-30C (59-86F)
- Avoid freezing and excessive heat above 40C (104F)

Inactive ingredients

Primary Alcobol Ethoxylate
Coconut Diethanol Amide
Sodium acetate trihydrate
Kathon.cmit/mit
Purity Water

Package Label - Principal Display Panel

2 L NDC: 74974-012-01